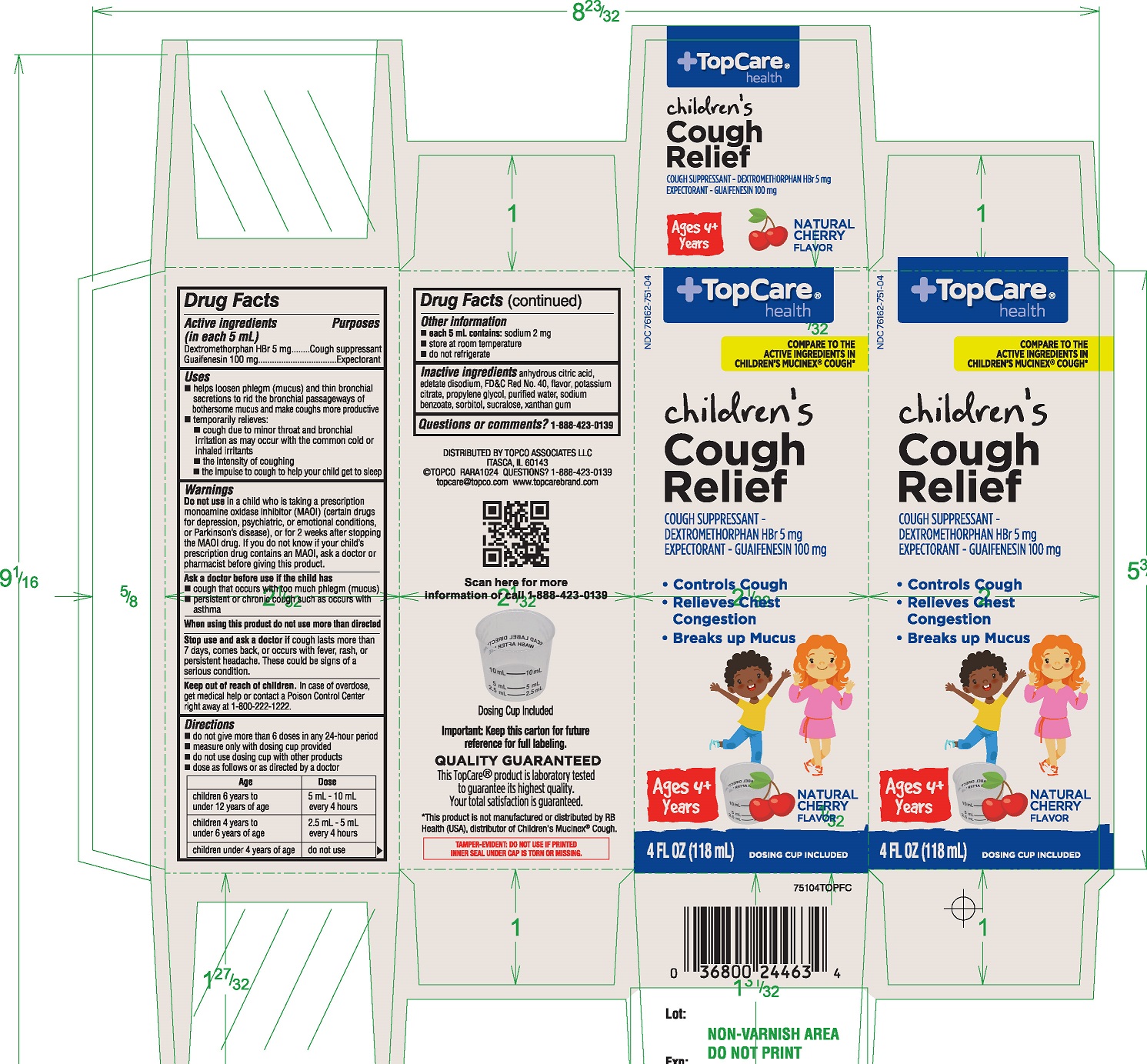 DRUG LABEL: TopCare Antifungal
NDC: 36800-754 | Form: LIQUID
Manufacturer: TOPCO ASSOCIATES LLC
Category: otc | Type: HUMAN OTC DRUG LABEL
Date: 20251222

ACTIVE INGREDIENTS: UNDECYLENIC ACID 25 mg/30 mL
INACTIVE INGREDIENTS: ISOPROPYL PALMITATE

TopCare® Maximum Strength Antifungal Liquid Solution

Active ingredient

Undecylenic Acid 25%

Purpose

Anti-fungal

Uses

- Proven effective in the treatment of most athlete’s foot (tinea pedis) and ringworm (tinea corporis)
- For effective relief of itching, burning and cracking.

Warnings

For external use only

Do not use

on children 2 years of age unless directed by a doctor.

When using this product

- avoid contact with eyes

Stop use and consult a doctor if

- there is no improvement within 4 weeks
- irritation occurs

KEEP THIS AND ALL MEDICATION OUT OF REACH OF CHILDREN.

If case of accidental ingestion, contact a physician, emergency medical care facility, or Poison Control Center immediately for advice at 1-800-222-1222.

Directions

Read all warnings and directions. Use only as directed.

- clean the affected area with soap and warm water and dry thoroughly.
- Apply a thin layer of Anti-Fungal liquid solution over affected area twice daily (morning and night) or as directed by a doctor.
- The brush applicator allows for easy application under nails and surrounding cuticle area.
- wear well-fitting, ventilated shoes, and change shoes and socks at least once daily.
- for athlete's foot: pay special attention to spaces between toes.
- For athlete's foot and ringworm, use daily for 4 weeks. If conditions persists longer, consult a doctor .
- this product is not effective on the scalp or nails.
- Supervise children in the use of this product.

Other information

- Store at room temperature 15°-30°C (59° - 86°F).
- Protect from freezing. If freezing occurs warm to room temperature.

Inactive ingredient

Isopropyl palmitate

Questions?

Call 1-888-423-0139

Principal Display Panel

NDC 36800-754-01

COMPARE TO FUNGICURE® active ingredient*

MAXIMUM STRENGTH
Anti-Fungal Liquid

- Topical formula for toe and foot
- Stops most athlete’s foot fungus and ringworm
- Helps relieves related discomforts

1 FL OZ (30mL)

QUALITY GURANTEED

This Top Care® product is laboratory tested to guarantee its highest quality. Your total satisfaction is guaranteed.

Side Panel

How to Eliminate Fungus?

Toe fungus can affect the areas around the cuticles and the skin around the tip of the nails. Anti-fungal work on contact but do not penetrate the nail,

So make sure tom keep nails clipped and clean away flaky skin and nail keratin when treating affected areas.

Anti-Fungal Liquid solution gets into hard to reach places, right where it’s needed, to treat fungus and stop it from spreading.

When will you see results?

- Anti-Fungal Liquid begins working immediately to eliminate toe and athlete’s foot fungus.
- You should begin to see results in 4 weeks.
- You may need to continue treating to allow for regrowth of healthy new tissue.

*This product is not manufactured or distributed by Alva-Amco Pharmacal Companies, the distributor of FungiCure®.

DISTRIBUTED BY

TOPCO ASSOCIATES LLC

ELKGROVE VILLAGE, IL 60007

© TOPCO RSE515

QUESTIONS? 1-888-423-0139

topcare@topco.com

www.topcarebrand.com